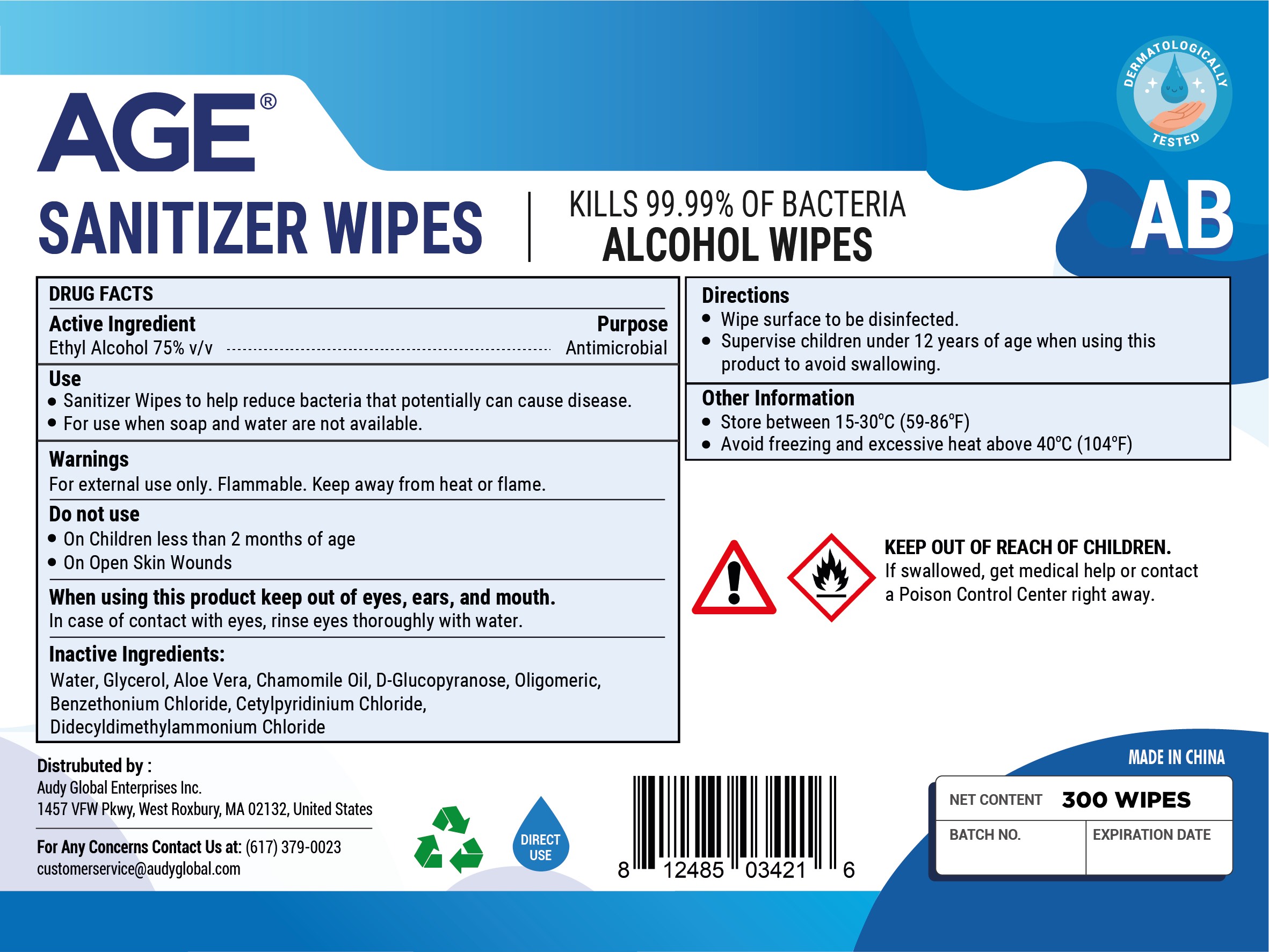 DRUG LABEL: Sanitizer Wipes
NDC: 75778-004 | Form: SOLUTION
Manufacturer: Audy Global Enterprises Inc.
Category: otc | Type: HUMAN OTC DRUG LABEL
Date: 20200527

ACTIVE INGREDIENTS: ALCOHOL 75 1/100 1
INACTIVE INGREDIENTS: DECYL GLUCOSIDE 0.1 1/100 1; CETYLPYRIDINIUM CHLORIDE ANHYDROUS 0.05 1/100 1; DIDECYLDIMONIUM CHLORIDE 0.04 1/100 1; GLYCERIN 0.5 1/100 1; ALOE VERA LEAF 0.3 1/100 1; CHAMAEMELUM NOBILE FLOWER OIL 0.2 1/100 1; BENZETHONIUM CHLORIDE 0.08 1/100 1; WATER 23.73 1/100 1

Active Ingredient(s)

Ethyl Alcohol 75% v/v.

Purpose

Purpose: Antimicrobial

Use

Sanitizer Wipes to help reduce bacteria that potentially can cause disease. For use when soap and water are not available.

Warnings

For external use only. Flammable. Keep away from heat or flame

Do not use

- On children less than 2 months of age
- On open skin wounds

When using this product keep out of eyes, ears, and mouth. In case of contact with eyes, rinse eyes thoroughly with water.

Keep out of reach of children. If swallowed, get medical help or contact a Poison Control Center right away.

Directions

Wipe surface to be disinfected.

Supervise children under 12 years of age when using this product to avoid swallowing.

Other information

- Store between 15-30C (59-86F)
- Avoid freezing and excessive heat above 40C (104F)

Inactive ingredients

Water Glycerol, Aloe. Vera, Chamomile Oil, D-Glucopyranose, Oligomeric, Benzethonium Chloride, Cetylpyridinium Chloride, Didecyldimethylammonium Chloride

Package Label - Principal Display Panel

300 units NDC:75778-004-30